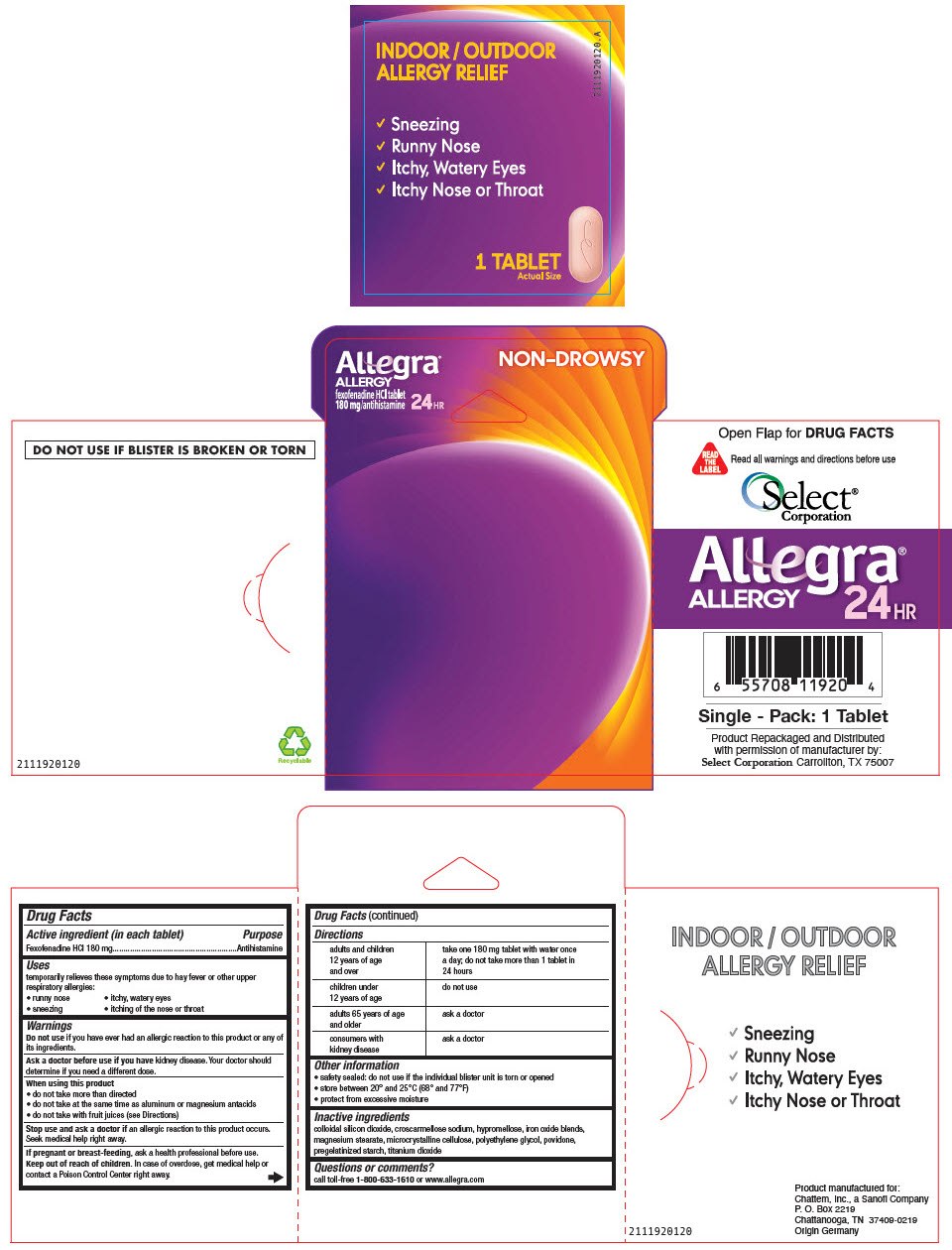 DRUG LABEL: Allegra Allergy 24 hour
NDC: 85237-0190 | Form: TABLET, FILM COATED
Manufacturer: Select Consumer Group
Category: otc | Type: HUMAN OTC DRUG LABEL
Date: 20250211

ACTIVE INGREDIENTS: FEXOFENADINE HYDROCHLORIDE 180 mg/1 1
INACTIVE INGREDIENTS: POVIDONE, UNSPECIFIED; HYPROMELLOSES; MAGNESIUM STEARATE; MICROCRYSTALLINE CELLULOSE; CROSCARMELLOSE SODIUM; TITANIUM DIOXIDE; BROWN IRON OXIDE; STARCH, CORN; SILICON DIOXIDE; POLYETHYLENE GLYCOL, UNSPECIFIED

Product Repackaged and Distributed
with permission of manufacturer by:
Select Corporation Carrollton, TX 75007

INACTIVE INGREDIENT

colloidal silicon dioxide, croscarmellose sodium, hypromellose, iron oxide blends, magnesium stearate, microcrystalline cellulose, polyethylene glycol, povidone, pregelatinized starch, titanium dioxide

ACTIVE INGREDIENT

Fexofenadine HCl 180 mg

Do not use if you have ever had an allergic reaction to this product or any of its ingredients.

Ask a doctor before use if you have kidney disease. Your doctor should determine if you need a different dose.

When using this product

do not take more than directed
do not take at the same time as aluminum or magnesium antacids
do not take with fruit juices (see Directions)

Stop use and ask a doctor if an allergic reaction to this product occurs. Seek medical help right away.

If pregnant or breast-feeding, ask a health professional before use.

Keep out of reach of children. In case of overdose, get medical help or contact a Poison Control Center right away.

DOSAGE AND ADMINISTRATION

adults and children 12 years of age and over take one 180 mg tablet with water once a day; do not take more than 1 tablet in 24 hours
children under 12 years of age do not use
adults 65 years of age and older ask a doctor
consumers with kidney disease ask a doctor

QUESTIONS

call toll-free 1-800-633-1610 or www.allegra.com

OTHER SAFETY INFORMATION

safety sealed: do not use if the individual blister unit is torn or opened
store between 20° and 25°C (68° and 77°F)
protect from excessive moisture

INDICATIONS AND USAGE

Antihistamine

Keep out of reach of children. In case of overdose, get medical help or contact a Poison Control Center right away.

PURPOSE

temporarily relieves these symptoms due to hay fever or other upper respiratory allergies:

runny nose
itchy, watery eyes
sneezing
itching of the nose or throat

PREGNANCY OR BREAST FEEDING

If pregnant or breast-feeding, ask a health professional before use.

HOW SUPPLIED

Supplied as one solid tablet of Fexondendaine Hcl 180mg

PACKAGE LABEL

Allegra®
ALLERGY
fexofenadine HCl tablet
180 mg/antihistamine
24HR

NON-DROWSY

INDOOR / OUTDOOR
ALLERGY RELIEF

2111920120.A

✓Sneezing
✓Runny Nose
✓Itchy, Watery Eyes
✓Itchy Nose or Throat

1 TABLET
Actual Size